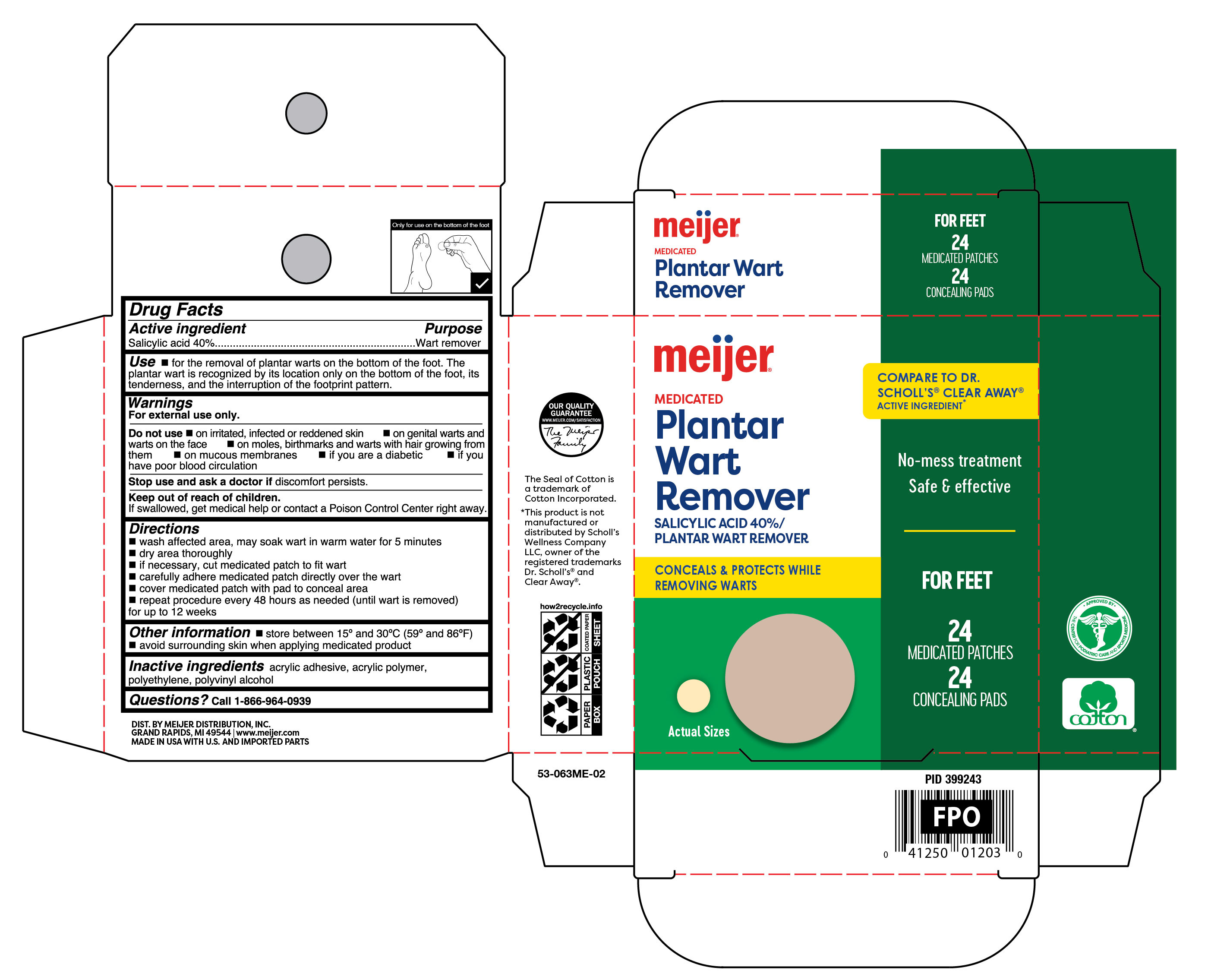 DRUG LABEL: Medicated Plantar Wart Remover
NDC: 79481-0619 | Form: PATCH
Manufacturer: Meijer Distribution Inc
Category: otc | Type: HUMAN OTC DRUG LABEL
Date: 20260102

ACTIVE INGREDIENTS: SALICYLIC ACID 400 mg/1 g
INACTIVE INGREDIENTS: POLYVINYL ALCOHOL, UNSPECIFIED; HIGH DENSITY POLYETHYLENE

Meijer Medicated Plantar Wart Remover

Active ingredient

Salicylic acid 40%

Purpose

Wart remover

Uses

- for the removal of plantar warts on the bottom of the foot. The plantar wart is recognized by its location only on the bottom of the foot, its tenderness, and the interruption of the footprint pattern.

Warnings

For external use only.

Do not use

- on irritated, infected or reddened skin
- on genital warts and warts on the face
- on moles, birthmarks and warts with hair growing from them
- on mucous membranes
- if you are diabetic
- if you have have poor blood circulation

Keep this and all drugs out of the reach of children.

If swallowed, get medical help or contact a Poison Control Center right away.

If discomfort persists

see your doctor or podiatrist.

Directions

- wash affected area, may soak wart in warm water for 5 minutes
- dry area thoroughly
- if necessary, cut medicated patches to fit wart
- apply the adhesive side of patch onto wart
- cover patch with pads to conceal area
- repeat procedure every 48 hours as needed (until wart is removed) for up to 12 weeks

Other information

store between 59° and 86°F (15° and 30°C)

Inactive ingredients

acrylic adhesive, acrylic polymer, polyethylene, polyvinyl alcohol

Questions?

call 1-866-964-0939

Principal Display Panel

meijer

Medicated

Plantar

Wart

Remover

Salicylic Acid 40%/Plantar Wart Remover

- Conceals and Protects while removing warts
- No-mess treatment
- safe & effective

For feet

24 Medicated Patches 24 Concealing Pads